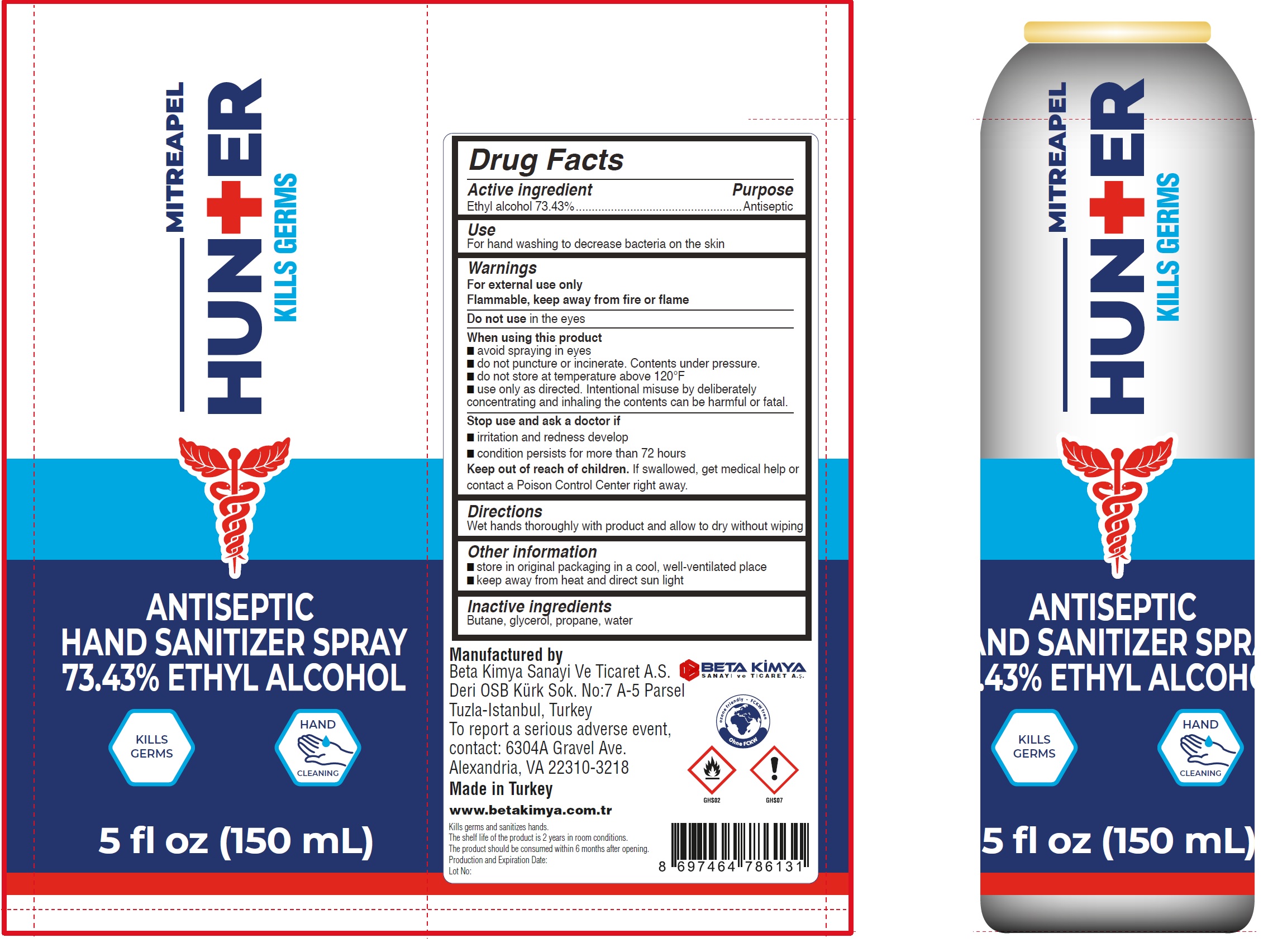 DRUG LABEL: Mitreapel Hunter Antiseptic Hand Sanitizer
NDC: 79932-001 | Form: AEROSOL, SPRAY
Manufacturer: BETA KIMYA SANAYI VE TICARET ANONIM SIRKETI
Category: otc | Type: HUMAN OTC DRUG LABEL
Date: 20200922

ACTIVE INGREDIENTS: ALCOHOL 0.7343 mL/1 mL
INACTIVE INGREDIENTS: BUTANE; GLYCERIN; PROPANE; WATER

Mitreapel Hunter Antiseptic Hand Sanitizer

Active ingredient

Ethyl alcohol 73.43%

Purpose

Antiseptic

Use

For hand washing to decrease bacteria on the skin

Warnings

For external use only
Flammable, keep away from fire or flame

Do not use

in the eyes

When using this product

- avoid spraying in eyes
- do not puncture or incinerate. Contents under pressure.
- do not store at temperature above 120°F
- use only as directed. Intentional misuse by deliberately concentrating and inhaling the contents can be harmful or fatal.

Stop use and ask a doctor if

- irritation and redness develop
- condition persists for more than 72 hours

Keep out of reach of children.

If swallowed, get medical help or contact a Poison Control Center right away.

Directions

Wet hands thoroughly with product and allow to dry without wiping

Other information

- store in original packaging in a cool, well-ventilated place
- keep away from heat and direct sun light

Inactive ingredients

Butane, glycerol, propane, water